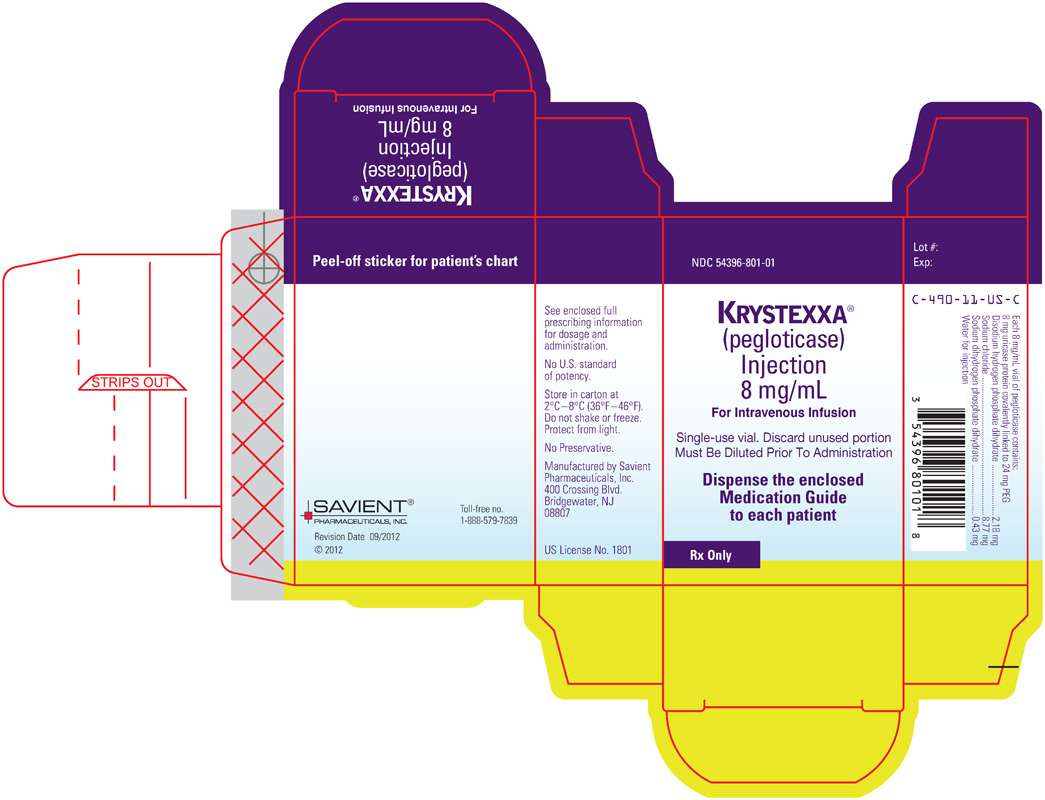 DRUG LABEL: Krystexxa
NDC: 54396-801 | Form: INJECTION, SOLUTION
Manufacturer: Savient Pharmaceuticals, Inc.
Category: prescription | Type: HUMAN PRESCRIPTION DRUG LABEL
Date: 20120915

ACTIVE INGREDIENTS: PEGLOTICASE 8 mg/1 mL
INACTIVE INGREDIENTS: SODIUM PHOSPHATE, DIBASIC, DIHYDRATE; SODIUM CHLORIDE; SODIUM PHOSPHATE, MONOBASIC, DIHYDRATE; WATER

HIGHLIGHTS OF PRESCRIBING INFORMATION

These highlights do not include all the information needed to use KRYSTEXXA safely and effectively. See full prescribing information for KRYSTEXXA
KRYSTEXXA® (pegloticase)
Injection, for intravenous infusion
Initial U.S. Approval: 2010

RECENT MAJOR CHANGES

- Dosage and Administration, Administration (2.3) 4/2012
- Warnings and Precautions, Anaphylaxis (5.1) 4/2012
- Warnings and Precautions, Infusion Reaction (5.2) 4/2012

WARNING: ANAPHYLAXIS AND INFUSION REACTIONS

See full prescribing information for complete boxed warning.

- Anaphylaxis and infusion reactions have been reported to occur during and after administration of KRYSTEXXA (5.1, 5.2).
- KRYSTEXXA should be administered in healthcare settings and by healthcare providers prepared to manage anaphylaxis and infusion reactions.
- Patients should be pre-medicated with antihistamines and corticosteroids.
- Patients should be closely monitored for an appropriate period of time for anaphylaxis after administration of KRYSTEXXA.
- Monitor serum uric acid levels prior to infusions and consider discontinuing treatment if levels increase to above 6 mg/dL, particularly when 2 consecutive levels above 6 mg/dL are observed.

1 INDICATIONS AND USAGE

KRYSTEXXA® (pegloticase) is a PEGylated uric acid specific enzyme indicated for the treatment of chronic gout in adult patients refractory to conventional therapy. (1)

Important Limitations of Use:

KRYSTEXXA is not recommended for the treatment of asymptomatic hyperuricemia. (1)

2 DOSAGE AND ADMINISTRATION

- For adult patients 8 mg given as an intravenous infusion every two weeks. (2.1)
- Do not administer as an intravenous push or bolus. (2.3)
- Discontinue oral urate-lowering agents before starting KRYSTEXXA (2.3)
- Monitor serum uric acid levels before each infusion. (2.3)
- Patients should be pre-medicated with antihistamines and corticosteroids. (2.3, 5.1, 5.2)
- Administer in a healthcare setting by healthcare providers prepared to manage anaphylaxis. (2.3, 5.1, 5.2)
- The KRYSTEXXA admixture should only be administered by intravenous infusion over no less than 120 minutes via gravity feed, syringe-type pump, or infusion pump. (2.3)

3 DOSAGE FORMS AND STRENGTHS

- 1 mL sterile concentrate for dilution containing 8 mg of pegloticase protein, expressed in uricase protein amounts. (3)

4 CONTRAINDICATIONS

- Glucose-6-phosphate dehydrogenase (G6PD) Deficiency: Before starting KRYSTEXXA, patients at higher risk for G6PD deficiency (e.g., those of African and Mediterranean ancestry) should be screened due to the risk of hemolysis and methemoglobinemia. (4)

5 WARNINGS AND PRECAUTIONS

- Anaphylaxis: Anaphylaxis occurred in patients treated with KRYSTEXXA. Anaphylaxis may occur with any infusion, including a first infusion, and generally manifests within 2 hours of the infusion. However, delayed-type hypersensitivity reactions have also been reported. KRYSTEXXA should be administered in healthcare settings and by healthcare providers prepared to manage anaphylaxis. Patients should be pre-medicated with antihistamines and corticosteroids. Patients should be closely monitored for an appropriate period of time for anaphylaxis after administration of KRYSTEXXA. (5.1)
- Infusion Reactions: Infusion reactions occurred in patients treated with KRYSTEXXA. KRYSTEXXA should be administered in a healthcare setting and by healthcare providers prepared to manage infusion reactions. Patients should be pre-medicated with antihistamines and corticosteroids. Monitor patients closely for signs and symptoms of infusion reactions. In the event of an infusion reaction, the infusion should be slowed, or stopped and restarted at a slower rate. If a severe infusion reaction occurs, discontinue infusion and institute treatment as needed. The risk of an infusion reaction is higher in patients who have lost therapeutic response. (5.2)
- Gout Flares: An increase in gout flares is frequently observed upon initiation of anti-hyperuricemic therapy, including treatment with KRYSTEXXA. If a gout flare occurs during treatment, KRYSTEXXA need not be discontinued. Gout flare prophylaxis (i.e., non-steroidal anti-inflammatory drugs [NSAID] or colchicine upon initiation of treatment) is recommended for at least the first 6 months of therapy unless medically contraindicated or not tolerated. (5.3)
- Congestive Heart Failure: KRYSTEXXA has not been formally studied in patients with congestive heart failure, but some patients in clinical trials experienced exacerbation. Exercise caution when using KRYSTEXXA in patients who have congestive heart failure and monitor patients closely following infusion. (5.4)

6 ADVERSE REACTIONS

The most common adverse reactions (occurring in at least 5% of KRYSTEXXA-treated patients) are gout flares, infusion reactions, nausea, contusion or ecchymosis, nasopharyngitis, constipation, chest pain, anaphylaxis and vomiting. (6.1)

To report SUSPECTED ADVERSE REACTIONS, contact Savient Pharmaceuticals, Inc. at 1-888-579-7839 (1-888-KRYSTEXXA) or FDA at 1-800-FDA-1088 or www.fda.gov/medwatch.

FULL PRESCRIBING INFORMATION

WARNING: ANAPHYLAXIS AND INFUSION REACTIONS

- Anaphylaxis and infusion reactions have been reported to occur during and after administration of KRYSTEXXA. [see Warnings and Precautions (5.1, 5.2)]
- Anaphylaxis may occur with any infusion, including a first infusion, and generally manifests within 2 hours of the infusion. However, delayed-type hypersensitivity reactions have also been reported.
- KRYSTEXXA should be administered in healthcare settings and by healthcare providers prepared to manage anaphylaxis and infusion reactions.
- Patients should be premedicated with antihistamines and corticosteroids.
- Patients should be closely monitored for an appropriate period of time for anaphylaxis after administration of KRYSTEXXA.
- Monitor serum uric acid levels prior to infusions and consider discontinuing treatment if levels increase to above 6 mg/dL, particularly when 2 consecutive levels above 6 mg/dL are observed.

1 INDICATIONS AND USAGE

KRYSTEXXA® (pegloticase) is a PEGylated uric acid specific enzyme indicated for the treatment of chronic gout in adult patients refractory to conventional therapy.

Gout refractory to conventional therapy occurs in patients who have failed to normalize serum uric acid and whose signs and symptoms are inadequately controlled with xanthine oxidase inhibitors at the maximum medically appropriate dose or for whom these drugs are contraindicated.

Important Limitations of Use:
KRYSTEXXA is not recommended for the treatment of asymptomatic hyperuricemia.

2 DOSAGE AND ADMINISTRATION

2.1 Dosage

The recommended dose and regimen of KRYSTEXXA for adult patients is 8 mg (uricase protein) given as an intravenous infusion every two weeks.

The optimal treatment duration with KRYSTEXXA has not been established.

2.2 Preparation

Visually inspect KRYSTEXXA for particulate matter and discoloration before administration, whenever solution and container permit. Do not use vials if either is present. [see Dosage Forms and Strengths (3)]

Use appropriate aseptic technique. Withdraw 1 mL of KRYSTEXXA from the vial into a sterile syringe. Discard any unused portion of product remaining in the 2 mL vial. Inject into a single 250 mL bag of 0.9% Sodium Chloride Injection, USP or 0.45% Sodium Chloride Injection, USP for intravenous infusion. Do not mix or dilute with other drugs.

Invert the infusion bag containing the dilute KRYSTEXXA solution a number of times to ensure thorough mixing. Do not shake.

KRYSTEXXA diluted in infusion bags is stable for 4 hours at 2° to 8°C (36° to 46°F) and at room temperature (20° to 25°C, 68° to 77°F). However it is recommended that diluted solutions be stored under refrigeration, not frozen, protected from light, and used within 4 hours of dilution. [see How Supplied/Storage and Handling (16)]

Before administration, allow the diluted solution of KRYSTEXXA to reach room temperature. KRYSTEXXA in a vial or in an intravenous infusion fluid should never be subjected to artificial heating (e.g., hot water, microwave).

2.3 Administration

Do not administer as an intravenous push or bolus.

It is recommended that before starting KRYSTEXXA patients discontinue oral urate-lowering medications and not institute therapy with oral urate-lowering agents while patients are on KRYSTEXXA therapy.

Monitoring Therapy: The risk of anaphylaxis and infusion reactions is higher in patients who have lost therapeutic response. Monitor serum uric acid levels prior to infusions and consider discontinuing treatment if levels increase to above 6 mg/dL, particularly when 2 consecutive levels above 6 mg/dL are observed. [see Warnings and Precautions (5.1, 5.2)]

The KRYSTEXXA admixture should only be administered by intravenous infusion over no less than 120 minutes via gravity feed, syringe-type pump, or infusion pump.

Patients should receive pre-infusion medications (e.g. antihistamines, corticosteroids), to minimize the risk of anaphylaxis and infusion reactions. Administer KRYSTEXXA in a healthcare setting and by healthcare providers prepared to manage anaphylaxis and infusion reactions, and observe patients for an appropriate period of time after administration. [see Warnings and Precautions (5.1, 5.2)]

If an infusion reaction occurs during the administration of KRYSTEXXA, the infusion may be slowed, or stopped and restarted at a slower rate, at the discretion of the physician. Since infusion reactions can occur after completion of infusion, observation of patients for approximately an hour post-infusion should be considered. [see Warnings and Precautions (5.2), Adverse Reactions (6.1)]

3 DOSAGE FORMS AND STRENGTHS

KRYSTEXXA is a clear, colorless, sterile 8 mg/mL solution of pegloticase in a 2 mL single-use vial, expressed as amounts of uricase protein. KRYSTEXXA must be diluted prior to use.

4 CONTRAINDICATIONS

Glucose-6-phosphate dehydrogenase (G6PD) deficiency: KRYSTEXXA is contraindicated in patients with G6PD deficiency due to the risk of hemolysis and methemoglobinemia. It is recommended that patients at higher risk for G6PD deficiency (e.g., patients of African or Mediterranean ancestry) be screened for G6PD deficiency before starting KRYSTEXXA.

5 WARNINGS AND PRECAUTIONS

5.1 Anaphylaxis

During pre-marketing controlled clinical trials, anaphylaxis was reported with a frequency of 6.5% of patients treated with KRYSTEXXA every 2 weeks, compared to none with placebo. Manifestations included wheezing, peri-oral or lingual edema, or hemodynamic instability, with or without rash or urticaria. Cases occurred in patients being pre-treated with one or more doses of an oral antihistamine, an intravenous corticosteroid and/or acetaminophen. This pre-treatment may have blunted or obscured symptoms or signs of anaphylaxis and therefore the reported frequency may be an underestimate. [See Adverse Reactions (6)]

KRYSTEXXA should be administered in a healthcare setting by healthcare providers prepared to manage anaphylaxis. Patients should be pre-treated with antihistamines and corticosteroids. Anaphylaxis may occur with any infusion, including a first infusion, and generally manifests within 2 hours of the infusion. However, delayed type hypersensitivity reactions have also been reported. Patients should be closely monitored for an appropriate period of time for anaphylaxis after administration of KRYSTEXXA. Patients should be informed of the symptoms and signs of anaphylaxis and instructed to seek immediate medical care should anaphylaxis occur after discharge from the healthcare setting.

The risk of anaphylaxis is higher in patients whose uric acid level increases to above 6 mg/dL, particularly when 2 consecutive levels above 6 mg/dL are observed. Monitor serum uric acid levels prior to infusions and consider discontinuing treatment if levels increase to above 6 mg/dL. Because of the possibility that concomitant use of oral urate-lowering therapy and KRYSTEXXA may potentially blunt the rise of serum uric acid levels, it is recommended that before starting KRYSTEXXA patients discontinue oral urate-lowering medications and not institute therapy with oral urate-lowering agents while taking KRYSTEXXA.

5.2 Infusion Reactions

During pre-marketing controlled clinical trials, infusion reactions were reported in 26% of patients treated with KRYSTEXXA 8 mg every 2 weeks, and 41% of patients treated with KRYSTEXXA 8 mg every 4 weeks, compared to 5% of patients treated with placebo. These infusion reactions occurred in patients being pre-treated with an oral antihistamine, intravenous corticosteroid and/or acetaminophen. This pre-treatment may have blunted or obscured symptoms or signs of infusion reactions and therefore the reported frequency may be an underestimate. [See Adverse Reactions (6)]

KRYSTEXXA should be administered in a healthcare setting by healthcare providers prepared to manage infusion reactions. Patients should be pre-treated with antihistamines and corticosteroids. KRYSTEXXA should be infused slowly over no less than 120 minutes. In the event of an infusion reaction, the infusion should be slowed, or stopped and restarted at a slower rate.

The risk of infusion reaction is higher in patients whose uric acid level increases to above 6 mg/dL, particularly when 2 consecutive levels above 6 mg/dL are observed. Monitor serum uric acid levels prior to infusions and consider discontinuing treatment if levels increase to above 6 mg/dL. Because of the possibility that concomitant use of oral urate-lowering therapy and KRYSTEXXA may potentially blunt the rise of serum uric acid levels, it is recommended that before starting KRYSTEXXA patients discontinue oral urate-lowering medications and not institute therapy with oral urate-lowering agents while taking KRYSTEXXA.

5.3 Gout Flares

Gout flares may occur after initiation of KRYSTEXXA. [see Adverse Reactions (6.1)] An increase in gout flares is frequently observed upon initiation of anti-hyperuricemic therapy, due to changing serum uric acid levels resulting in mobilization of urate from tissue deposits. Gout flare prophylaxis with a non-steroidal anti-inflammatory drug (NSAID) or colchicine is recommended starting at least 1 week before initiation of KRYSTEXXA therapy and lasting at least 6 months, unless medically contraindicated or not tolerated. KRYSTEXXA does not need to be discontinued because of a gout flare. The gout flare should be managed concurrently as appropriate for the individual patient. [see Dosage and Administration (2)]

5.4 Congestive Heart Failure

KRYSTEXXA has not been formally studied in patients with congestive heart failure, but some patients in the clinical trials experienced exacerbation. [see Adverse Reactions (6.1)] Exercise caution when using KRYSTEXXA in patients who have congestive heart failure and monitor patients closely following infusion.

5.5 Re-treatment with KRYSTEXXA

No controlled trial data are available on the safety and efficacy of re-treatment with KRYSTEXXA after stopping treatment for longer than 4 weeks. Due to the immunogenicity of KRYSTEXXA, patients receiving re-treatment may be at increased risk of anaphylaxis and infusion reactions. Therefore, patients receiving re-treatment after a drug-free interval should be monitored carefully. [see Adverse Reactions (6.2)]

6 ADVERSE REACTIONS

The most commonly reported serious adverse reactions from pre-marketing controlled clinical trials were anaphylaxis, which occurred at a frequency of 6.5% in patients treated with KRYSTEXXA 8 mg every 2 weeks, compared to none with placebo; infusion reactions, which occurred at a frequency of 26% in patients treated with KRYSTEXXA 8 mg every 2 weeks, compared to 5% treated with placebo; and gout flares, which were more common during the first 3 months of treatment with KRYSTEXXA compared with placebo. All patients in pre-marketing controlled clinical trials were pre-treated with an oral antihistamine, intravenous corticosteroid and/or acetaminophen to prevent anaphylaxis and infusion reaction. Patients also received non-steroidal anti-inflammatory drugs or colchicine, or both, for at least 7 days as gout flare prophylaxis before beginning KRYSTEXXA treatment. [see Boxed Warning, Warnings and Precautions (5.1, 5.2, 5.3)]

6.1 Clinical Trials Experience

The data described below reflect exposure to KRYSTEXXA in patients with chronic gout refractory to conventional therapy in two replicate randomized, placebo-controlled, double-blind 6-month clinical trials: 85 patients were treated with KRYSTEXXA 8 mg every 2 weeks; 84 patients were treated with KRYSTEXXA 8 mg every 4 weeks; and 43 patients were treated with placebo. These patients were between the ages of 23 and 89 years (average 55 years); 173 patients were male and 39 were female; and 143 patients were White/Caucasian, 27 were Black/African American, 24 were Hispanic/Latino and 18 were all other ethnicities. Common co-morbid conditions among the enrolled patients included hypertension (72%), dyslipidemia (49%), chronic kidney disease (28%), diabetes (24%), coronary artery disease (18%), arrhythmia (16%), and cardiac failure/left ventricular dysfunction (12%).

Because clinical studies are conducted under widely varying and controlled conditions, adverse reaction rates observed in clinical studies of a drug cannot be directly compared to rates in the clinical studies of another drug, and may not predict the rates observed in a broader patient population in clinical practice.

Anaphylaxis:

Diagnostic criteria of anaphylaxis were skin or mucosal tissue involvement, and, either airway compromise, and/or reduced blood pressure with or without associated symptoms, and a temporal relationship to KRYSTEXXA or placebo injection with no other identifiable cause. Using these clinical criteria, anaphylaxis was identified in 14 (5.1%) of 273 total patients studied in the clinical program of IV KRYSTEXXA. The frequency was 6.5% for the every 2-week dosing regimen (8 of 123 patients), and 4.8% for the 4-week dosing frequency (6 of 126) of KRYSTEXXA. There were no cases of anaphylaxis in patients receiving placebo. Anaphylaxis generally occurred within 2 hours after treatment. This occurred with patients being pre-treated with an oral antihistamine, intravenous corticosteroid, and acetaminophen. [see Boxed Warning, Warnings and Precautions (5.1, 5.2)]

Infusion Reactions:

Infusion reactions occurred in 26% of patients in the 2 week dosing regimen group and 41% of patients in the 4 week dosing regimen group, compared to 5% of placebo-treated patients. Manifestations of these reactions included urticaria (frequency of 10.6%), dyspnea (frequency of 7.1%), chest discomfort (frequency of 9.5%), chest pain (frequency of 9.5%), erythema (frequency of 9.5%), and pruritus (frequency of 9.5%). These manifestations overlap with the symptoms of anaphylaxis, but in a given patient did not occur together to satisfy the clinical criteria for diagnosing anaphylaxis. Infusion reactions are thought to result from release of various mediators, such as cytokines. Infusion reactions occurred at any time during a course of treatment with approximately 3% occurring with the first infusion, and approximately 91% occurred during the time of infusion. Some infusion reaction manifestations were reduced with slowing the rate of infusion, or stopping the infusion and restarting the infusion at a slower rate. These infusion reactions occurred with all patients being pre-treated with an oral antihistamine, intravenous corticosteroid and acetaminophen. [see Boxed Warning, Warnings and Precautions (5.1, 5.2)]

Gout Flares:

Gout flares were common in the study patients before randomization to treatment, with patients experiencing an average of 10 flares in the preceding 18 months prior to study entry. During the controlled treatment period with KRYSTEXXA or placebo, the frequencies of gout flares were high in all treatment groups, but more so with KRYSTEXXA treatment during the first 3 months of treatment, which seemed to decrease in the subsequent 3 months of treatment. The percentages of patients with any flare for the first 3 months were 74%, 81%, and 51%, for KRYSTEXXA 8 mg every 2 weeks, KRYSTEXXA 8 mg every 4 weeks, and placebo, respectively. The percentages of patients with any flare for the subsequent 3 months were 41%, 57%, and 67%, for KRYSTEXXA 8 mg every 2 weeks, KRYSTEXXA 8 mg every 4 weeks, and placebo, respectively. Patients received gout flare prophylaxis with colchicine and/or nonsteroidal anti-inflammatory drugs (NSAIDs) starting at least one week before receiving KRYSTEXXA. [see Warnings and Precautions (5.3)]

Congestive Heart Failure:

Two cases of congestive heart failure exacerbation occurred during the trials in patients receiving treatment with KRYSTEXXA 8 mg every 2 weeks. No cases were reported in placebo-treated patients. Four subjects had exacerbations of pre-existing congestive heart failure while receiving KRYSTEXXA 8 mg every 2 weeks during the open-label extension study. [see Warnings and Precautions (5.4)].

Other Adverse Reactions:

The most commonly reported adverse reactions that occurred in greater than or equal to 5% of patients treated with KRYSTEXXA 8 mg every 2 weeks are provided in Table 1.

Table 1. Adverse Reactions Occurring in 5% or More of Patients Treated with KRYSTEXXA Compared to Placebo
Adverse Reaction (Preferred Term) | KRYSTEXXA 8 mg every 2 weeks (N=85) Na (%) | Placebo (N=43) N (%)
Gout flare | 65 (77%) | 35 (81%)
Infusion reaction | 22 (26%) | 2 (5%)
Nausea | 10 (12%) | 1 (2%)
Contusionb or Ecchymosisb | 9 (11%) | 2 (5%)
Nasopharyngitis | 6 (7%) | 1 (2%)
Constipation | 5 (6%) | 2 (5%)
Chest Pain | 5 (6%) | 1 (2%)
Anaphylaxis | 4 (5%) | 0 (0%)
Vomiting | 4 (5%) | 1 (2%)
a If the same subject in a given group had more than one occurrence in the same preferred term event category, the subject was counted only once.
b Most did not occur on the day of infusion and could be related to other factors (e.g. concomitant medications relevant to contusion or ecchymosis, insulin dependent diabetes mellitus).

6.2 Immunogenicity

Anti-pegloticase antibodies developed in 92% of patients treated with KRYSTEXXA every 2 weeks, and 28% for placebo. Anti-PEG antibodies were also detected in 42% of patients treated with KRYSTEXXA. High anti-pegloticase antibody titer was associated with a failure to maintain pegloticase-induced normalization of uric acid. The impact of anti-PEG antibodies on patients' responses to other PEG-containing therapeutics is unknown.

There was a higher incidence of infusion reactions in patients with high anti-pegloticase antibody titer: 53% (16 of 30) in the KRYSTEXXA every 2 weeks group compared to 6% in patients who had undetectable or low antibody titers.

As with all therapeutic proteins, there is a potential for immunogenicity. The observed incidence of antibody positivity in an assay is highly dependent on several factors including assay sensitivity and specificity and assay methodology, sample handling, timing of sample collection, concomitant medications, and underlying disease. For these reasons, the comparison of the incidence of antibodies to pegloticase with the incidence of antibodies to other products may be misleading.

7 DRUG INTERACTIONS

No studies of interactions of KRYSTEXXA with other drugs have been conducted.

Because anti-pegloticase antibodies appear to bind to the PEG portion of the drug, there may be potential for binding with other PEGylated products. The impact of anti-PEG antibodies on patients' responses to other PEG-containing therapeutics is unknown.

8 USE IN SPECIFIC POPULATIONS

8.1 Pregnancy

Pregnancy Category C

A complete evaluation of the reproductive and developmental toxicity of pegloticase has not been completed. Adequate animal reproduction studies have not been conducted with KRYSTEXXA. It is not known whether KRYSTEXXA can cause fetal harm when administered to a pregnant woman or can affect reproductive capacity. There are no adequate and well-controlled studies in pregnant women. KRYSTEXXA should be used during pregnancy only if clearly needed.

Pegloticase was not teratogenic in rats administered 0, 5, 10, or 40 mg/kg twice weekly by the intravenous route on gestation days 6 through 16 (the doses are approximately 6-fold to 50-fold higher than the maximum recommended human dose (MRHD) of 8 mg (0.133 mg/kg based on a 60 kg person) every 2 weeks based on a mg/m^2 comparison).

8.3 Nursing Mothers

It is not known whether this drug is excreted in human milk. Because many drugs are excreted in human milk and because of the potential for serious adverse reactions in nursing infants, it is not recommended to administer KRYSTEXXA to a nursing mother.

8.4 Pediatric Use

The safety and effectiveness of KRYSTEXXA in pediatric patients less than 18 years of age have not been established.

8.5 Geriatric Use

Of the total number of patients treated with KRYSTEXXA 8 mg every 2 weeks in the controlled studies, 34% (29 of 85) were 65 years of age and older and 12% (10 of 85) were 75 years of age and older. No overall differences in safety or effectiveness were observed between older and younger patients, but greater sensitivity of some older individuals cannot be ruled out. No dose adjustment is needed for patients 65 years of age and older.

8.6 Renal Impairment

No dose adjustment is required for patients with renal impairment. A total of 32% (27 of 85) of patients treated with KRYSTEXXA 8 mg every 2 weeks had a creatinine clearance of ≤62.5 mL/min. No overall differences in efficacy were observed.

10 OVERDOSAGE

No reports of overdosage with KRYSTEXXA have been reported. The maximum dose that has been administered as a single intravenous dose is 12 mg as uricase protein.

Patients suspected of receiving an overdose should be monitored, and general supportive measures should be initiated as no specific antidote has been identified.

11 DESCRIPTION

KRYSTEXXA (pegloticase) is a uric acid specific enzyme which is a PEGylated product that consists of recombinant modified mammalian urate oxidase (uricase) produced by a genetically modified strain of Escherichia coli. Uricase is covalently conjugated to monomethoxypoly(ethylene glycol) [mPEG] (10 kDa molecular weight). The cDNA coding for uricase is based on mammalian sequences. Each uricase subunit has a molecular weight of approximately 34 kDa per subunit. The average molecular weight of pegloticase (tetrameric enzyme conjugated to mPEG) is approximately 540 kDa.

KRYSTEXXA is intended for intravenous infusion.

KRYSTEXXA is a sterile, clear, colorless solution containing 8 mg/mL pegloticase in phosphate-buffered saline.

KRYSTEXXA (pegloticase) concentrations are expressed as concentrations of uricase protein. Each mL of KRYSTEXXA contains 8 mg of uricase protein (conjugated to 24 mg of 10 kDa mPEG), 2.18 mg Disodium Hydrogen Phosphate Dihydrate (Na2HPO4•2H2O), 8.77 mg Sodium Chloride (NaCl), 0.43 mg Sodium Dihydrogen Phosphate Dihydrate (NaH2PO4•2H2O), and Water for Injection to deliver 8 mg of pegloticase (as uricase protein).

12 CLINICAL PHARMACOLOGY

12.1 Mechanism of Action

KRYSTEXXA is a uric acid specific enzyme which is a recombinant uricase and achieves its therapeutic effect by catalyzing the oxidation of uric acid to allantoin, thereby lowering serum uric acid. Allantoin is an inert and water soluble purine metabolite. It is readily eliminated, primarily by renal excretion.

12.2 Pharmacodynamics

Approximately 24 hours following the first dose of KRYSTEXXA, mean plasma uric acid levels for subjects in the KRYSTEXXA groups were 0.7 mg/dL for the KRYSTEXXA 8 mg every 2 weeks group. In comparison, the mean plasma uric acid level for the placebo group was 8.2 mg/dL.

In a single-dose, dose-ranging trial, following 1-hour intravenous infusions of 0.5, 1, 2, 4, 8 or 12 mg of pegloticase in 24 patients with symptomatic gout (n=4 subjects/dose group), plasma uric acid decreased with increasing pegloticase dose or concentrations. The duration of suppression of plasma uric acid appeared to be positively associated with pegloticase dose. Sustained decrease in plasma uric acid below the solubility concentration of 6 mg/dL for more than 300 hours was observed with doses of 8 mg and 12 mg.

12.3 Pharmacokinetics

Pegloticase levels were determined in serum based on measurements of uricase enzyme activity.

Following single intravenous infusions of 0.5 mg to 12 mg pegloticase in 23 patients with symptomatic gout, maximum serum concentrations of pegloticase increased in proportion to the dose administered.

The population pharmacokinetic analysis showed that age, sex, weight, and creatinine clearance did not influence the pharmacokinetics of pegloticase. Significant covariates included in the model for determining clearance and volume of distribution were found to be body surface area and anti-pegloticase antibodies.

The pharmacokinetics of pegloticase has not been studied in children and adolescents.

No formal studies were conducted to examine the effects of either renal or hepatic impairment on pegloticase pharmacokinetics.

13 NONCLINICAL TOXICOLOGY

13.1 Carcinogenesis, Mutagenesis, Impairment of Fertility

Long-term animal studies have not been performed to evaluate the carcinogenic potential of pegloticase.

The genotoxic potential of pegloticase has not been evaluated.

Fertility studies in animals have not been performed.

13.2 Animal Toxicology and/or Pharmacology

In a 12-week intravenous repeat-dose study in dogs, there was a dose-dependent increase in vacuolated macrophages in the spleen. The presence of vacuolated macrophages likely reflects accumulated removal of injected pegloticase (foreign) material from the circulation. There was no evidence of degeneration, inflammation, or necrosis associated with the vacuoles findings, however there was evidence of decreased functional response to liposaccharides.

In a 39-week, repeat dose dog study, there was a dose dependent increase in vacuolated cells in several organs, including the spleen, adrenal gland, liver, heart, duodenum and jejunum. In the spleen, liver, duodenum and jejunum, these vacuoles were within macrophages and most likely represented phagocytic removal of pegloticase from the circulation. However, the vacuolated cells in the heart and adrenal gland did not stain as macrophages. In the aortic outflow tract of the heart, vacuoles were in the cytoplasm of endothelial cells in the intimal lining of the aorta. In the adrenal gland, vacuoles were located within cortical cells in the zona reticularis and zona fasciculata. The clinical significance of these findings and the functional consequences are unknown.

14 CLINICAL STUDIES

The efficacy of KRYSTEXXA was studied in adult patients with chronic gout refractory to conventional therapy in two replicate, multicenter, randomized, double-blind, placebo-controlled studies of six months duration: Trial 1 and Trial 2. Patients were randomized to receive KRYSTEXXA 8 mg every 2 weeks or every 4 weeks or placebo in a 2:2:1 ratio. Studies were stratified for the presence of tophi. Seventy-one percent (71%) of patients had baseline tophi. All patients were prophylaxed with an oral antihistamine, intravenous corticosteroid and acetaminophen. Patients also received prophylaxis for gout flares with non-steroidal anti-inflammatory drugs (NSAIDs) or colchicine, or both, beginning at least one week before KRYSTEXXA treatment unless medically contraindicated or not tolerated. Patients who completed the randomized clinical trials were eligible to enroll in a 2-year open label extension study.

Entry criteria for patients to be eligible for the trials were: baseline serum uric acid (SUA) of at least 8 mg/dL; had symptomatic gout with at least 3 gout flares in the previous 18 months or at least 1 gout tophus or gouty arthritis; and had a self-reported medical contraindication to allopurinol or medical history of failure to normalize uric acid (to less than 6 mg/dL) with at least 3 months of allopurinol treatment at the maximum medically appropriate dose.

The mean age of study subjects was 55 years (23-89); 82% were male, mean body mass index (BMI) was 33 kg/m^2, mean duration of gout was 15 years, and mean baseline SUA was 10 mg/dL.

To assess the efficacy of KRYSTEXXA in lowering uric acid, the primary endpoint in both trials was the proportion of patients who achieved plasma uric acid (PUA) less than 6 mg/dL for at least 80% of the time during Month 3 and Month 6. As shown in Table 2, a greater proportion of patients treated with KRYSTEXXA every 2 weeks achieved urate lowering to below 6 mg/dL than patients receiving placebo. Although the 4 week regimen also demonstrated efficacy for the primary endpoint, this regimen was associated with increased frequency of anaphylaxis and infusion reactions and less efficacy with respect to tophi.

Table 2 Plasma Uric Acid < 6 mg/dL for at Least 80% of the Time During Months 3 and 6
Treatment Group | N | Number (%) of Subjects Who Met Response Criteria | 95% Confidence Interval^1 | P-Value^2
Trial 1
Pegloticase 8 mg every 2 weeks | 43 | 20 (47%) | [32%, 61%] | <0.001
Pegloticase 8 mg every 4 weeks | 41 | 8 (20%) | [7%, 32%] | 0.044
Placebo | 20 | 0 (0%)
Trial 2
Pegloticase 8 mg every 2 weeks | 42 | 16 (38%) | [23%, 53%] | <0.001
Pegloticase 8 mg every 4 weeks | 43 | 21 (49%) | [34%, 64%] | <0.001
Placebo | 23 | 0 (0%)
^1 95% confidence interval for differences in responder rate between pegloticase group vs. placebo
^2 P-value using Fisher's exact test to compare pegloticase group vs. placebo
Note: Based on post-hoc analyses of the clinical trial data, if KRYSTEXXA had been stopped when a patient's uric acid level rose to greater than 6 mg/dL on a single occasion, the incidence of infusion reactions would have been reduced by approximately 67%, but the success rates for the primary efficacy endpoint would have been reduced by approximately 20%. If KRYSTEXXA had been stopped after 2 consecutive uric acid levels greater than 6 mg/dL, the incidence of infusion reactions would have been half, and there would have been little change in the efficacy outcome.

The effect of treatment on tophi was a secondary efficacy endpoint and was assessed using standardized digital photography, image analysis, and a Central Reader blinded to treatment assignment. Approximately 70% of patients had tophi at baseline. A pooled analysis of data from Trial 1 and Trial 2 was performed as pre-specified in the protocols. At Month 6, the percentage of patients who achieved a complete response (defined as 100% resolution of at least one target tophus, no new tophi appear and no single tophus showing progression) was 45%, 26%, and 8%, with KRYSTEXXA 8 mg every 2 weeks, KRYSTEXXA 8 mg every 4 weeks, and placebo, respectively. The difference between KRYSTEXXA and placebo was statistically significant for the every 2 week dosing regimen, but not for the every 4 week dosing regimen.

16 HOW SUPPLIED/STORAGE AND HANDLING

How Supplied

KRYSTEXXA is supplied as a clear, colorless, sterile solution in phosphate buffered saline intended for intravenous infusion after dilution. KRYSTEXXA is supplied in a single-use 2 mL glass vial with a Teflon® coated (latex-free) rubber injection stopper to deliver KRYSTEXXA as 8 mg of uricase protein in 1 mL volume.

Storage and Handling

Before the preparation for use, KRYSTEXXA must be stored in the carton and maintained at all times under refrigeration between 2° to 8°C (36° to 46°F). Protect from light. Do not shake or freeze.

Do not use beyond the expiration date stamped.

NDC# 54396-801-01

17 PATIENT COUNSELING INFORMATION

See Medication Guide

17.1 General Information

Provide and instruct patients to read the accompanying Medication Guide before starting treatment and before each subsequent treatment.

17.2 Anaphylaxis and Infusion Reactions

- Anaphylaxis and infusion reactions can occur at any infusion while on therapy. Counsel patients on the importance of adhering to any prescribed medications to help prevent or lessen the severity of these reactions.
- Educate patients on the signs and symptoms of anaphylaxis, including wheezing, peri-oral or lingual edema, hemodynamic instability, and rash or urticaria.
- Educate patients on the most common signs and symptoms of an infusion reaction, including urticaria (skin rash), erythema (redness of the skin), dyspnea (difficulty breathing), flushing, chest discomfort, chest pain, and rash.
- Advise patients to seek medical care immediately if they experience any symptoms of an allergic reaction during or at any time after the infusion of KRYSTEXXA. [see Warnings and Precautions (5.1, 5.2), Adverse Reactions (6.1)]
- Advise patients to discontinue any oral urate-lowering agents before starting on KRYSTEXXA and not to take any oral urate-lowering agents while on KRYSTEXXA.

17.3 Glucose-6-phosphate dehydrogenase (G6PD) Deficiency

Inform patients not to take KRYSTEXXA if they have a condition known as G6PD deficiency. Explain to patients that G6PD deficiency is more frequently found in individuals of African or Mediterranean ancestry and that they may be tested to determine if they have G6PD deficiency, unless already known. [See Contraindications (4)]

17.4 Gout Flares

Explain to patients that gout flares may initially increase when starting treatment with KRYSTEXXA, and that medications to help reduce flares may need to be taken regularly for the first few months after KRYSTEXXA is started. [see Warnings and Precautions (5.3), Adverse Reactions (6.1)] Advise patients that they should not stop KRYSTEXXA therapy if they have a flare.

Manufactured by:
Savient Pharmaceuticals, Inc.
400 Crossing Boulevard
Bridgewater, NJ 08807

Medication Guide

KRYSTEXXA® (Phonetic spelling: Kris-TEX-a)

(pegloticase)

Injection

For Intravenous Infusion

Read this Medication Guide before you start receiving KRYSTEXXA and before each treatment. There may be new information. This Medication Guide does not take the place of talking with your doctor about your medical condition or treatment. Talk to your doctor if you have any questions about your treatment with KRYSTEXXA.

What is the most important information I should know about KRYSTEXXA?

Serious allergic reactions may happen in some people who receive KRYSTEXXA. These allergic reactions can be life threatening and usually happen within 2 hours of the infusion.

KRYSTEXXA should be given to you by a doctor or nurse in a healthcare setting where serious allergic reactions can be treated. Your doctor or nurse should watch you for any signs of a serious allergic reaction during and after your treatment with KRYSTEXXA.

Tell your doctor or nurse right away if you have any of these symptoms during or after your treatment with KRYSTEXXA:

- wheezing, shortness of breath, cough, chest tightness, chest pain, or trouble breathing
- dizziness, fainting, fast or weak heartbeat or feeling nervous
- reddening of the face, itching, hives, or feeling warm
- swelling of the throat or tongue, throat tightness, hoarse voice or trouble swallowing

What is KRYSTEXXA?

KRYSTEXXA is a prescription medicine used in adults to help reduce the signs and symptoms of gout that are not controlled by other treatments.

People with gout have too much uric acid in their bodies. Uric acid crystals collect in joints, kidneys, and other organs. This may cause pain, redness and swelling (inflammation). KRYSTEXXA works to lower blood levels of uric acid.

It is not known if KRYSTEXXA is safe and effective in children.

Who should not receive KRYSTEXXA?

Do not receive KRYSTEXXA if you have a rare blood problem called glucose 6-phosphate dehydrogenase (G6PD) deficiency or favism. Your doctor may test you for G6PD before you start KRYSTEXXA.

What should I tell my doctor before receiving treatment with KRYSTEXXA?

Before you receive KRYSTEXXA, tell your doctor if you:

- know you have G6PD deficiency
- ever had any heart problems or high blood pressure
- are pregnant or plan to become pregnant. It is not known if KRYSTEXXA will harm your unborn baby. Talk to your doctor if you are pregnant or plan to become pregnant.
- are breastfeeding or plan to breastfeed. It is not known if KRYSTEXXA passes into your breast milk. You and your doctor should decide if you will receive KRYSTEXXA or breastfeed.

Tell your doctor about all the medicines you take, including prescription and non-prescription medicines, vitamins, and herbal supplements. Do not take any other uric acid lowering drug, such as allopurinol or febuxostat (Uloric®), while taking KRYSTEXXA.

Know the medicines you take. Keep a list of your medicines and show them to your doctor and pharmacist when you get a new medicine.

How will I receive KRYSTEXXA?

- Your doctor may give you medicine before your treatment of KRYSTEXXA to help reduce your chance of getting a reaction. Take these medicines as directed by your doctor or nurse.
- You will receive KRYSTEXXA through a needle in your vein (i.v. infusion).
- Your treatment will take about 2 hours or sometimes longer. A doctor or nurse will give you the treatment.
- You will receive KRYSTEXXA every 2 weeks.
- If you have side effects, your doctor may stop or slow the infusion and may give you medicine to help the side effects.
- A doctor or nurse will watch you for side effects while you receive KRYSTEXXA and for some time afterwards.
- Your doctor may stop your KRYSTEXXA if your uric acid levels do not become normal and stay controlled or you have certain side effects.
- Your gout flares may increase in the first 3 months when you start receiving KRYSTEXXA. Do not stop receiving KRYSTEXXA even if you have a flare as the amount of flares will decrease after 3 months of treatment. Your doctor may give you other medicines to help reduce your gout flares for the first few months after starting KRYSTEXXA.

What are the possible side effects of KRYSTEXXA?

KRYSTEXXA may cause serious side effects. See "What is the most important information I should know about KRYSTEXXA?"

The most common side effects of KRYSTEXXA include:

- gout flares
- allergic reactions. See "What is the most important information I should know about KRYSTEXXA."
- bruising
- sore throat
- constipation
- chest pain
- vomiting

Tell your doctor if you have any side effect that bothers you or that does not go away.

These are not all of the side effects of KRYSTEXXA. For more information, ask your doctor or pharmacist.

Call your doctor for medical advice about side effects. You may report side effects to FDA at 1-800-FDA-1088.

You may also report side effects to Savient Pharmaceuticals at 1-888-579-7839.

General information about the safe and effective use of KRYSTEXXA

Medicines are sometimes prescribed for purposes other than those listed in a Medication Guide. This Medication Guide summarizes the most important information about KRYSTEXXA. If you would like more information, talk with your doctor. You can ask your pharmacist or doctor for information about KRYSTEXXA that is written for health professionals.

For more information, go to www.KRYSTEXXA.com or www.SAVIENT.com or call 1-888-579-7839.

What are the ingredients in KRYSTEXXA?

Active ingredient: pegloticase

Inactive ingredients: disodium hydrogen phosphate dihydrate, sodium chloride, sodium dihydrogen phosphate dihydrate, and water for injection.

Product manufactured by:
Savient Pharmaceuticals, Inc.
400 Crossing Boulevard
Bridgewater, NJ 08807

This Medication Guide has been approved by the U.S. Food and Drug Administration.

Code #: 1801
Revised: 04/2013

©2013 Savient Pharmaceuticals, Inc.

PACKAGE LABEL

PRINCIPAL DISPLAY PANEL

NDC 54396-801-01

KRYSTEXXA®
(pegloticase)
Injection
8 mg/mL
For Intravenous Infusion

Single-use vial. Discard unused portion
Must Be Diluted Prior To Administration

Dispense the enclosed Medication Guide to each patient

Rx Only

Lot #:
Exp:

C-490-11-US-C

Each 8 mg/mL vial of pegloticase contains:
8 mg uricase protein covalently linked to 24 mg PEG
Disodium hydrogen phosphate dihydrate...2.18 mg
Sodium chloride...8.77 mg
Sodium dihydrogen phosphate dihydrate...0.43 mg
Water for injection

See enclosed full prescribing information for dosage and administration.

No U.S. standard of potency.

Store in carton at 2°C-8°C (36°F-46°F).
Do not shake or freeze.
Protect from light.

No Preservative.

Manufactured by Savient Pharmaceuticals, Inc.
400 Crossing Blvd.
Bridgewater, NJ 08807

US License No. 1801

Peel-off sticker for patient's chart

SAVIENT®
PHARMACEUTICALS, INC.

Toll-free no.
1-888-579-7839

Revision Date 09/2012
© 2012